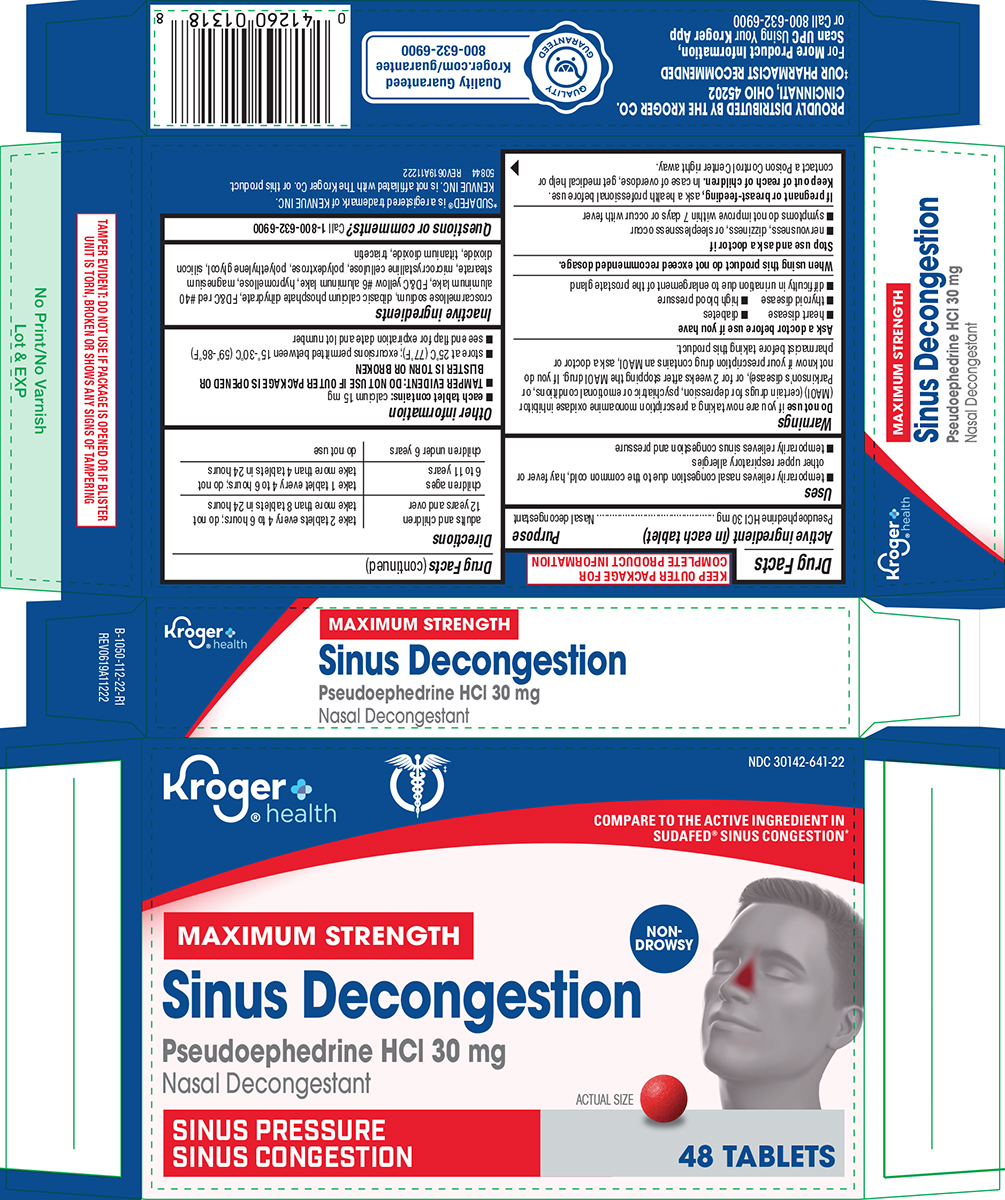 DRUG LABEL: Sinus Decongestion
NDC: 30142-641 | Form: TABLET, FILM COATED
Manufacturer: Kroger Company
Category: otc | Type: HUMAN OTC DRUG LABEL
Date: 20251124

ACTIVE INGREDIENTS: PSEUDOEPHEDRINE HYDROCHLORIDE 30 mg/1 1
INACTIVE INGREDIENTS: CROSCARMELLOSE SODIUM; DIBASIC CALCIUM PHOSPHATE DIHYDRATE; FD&C RED NO. 40 ALUMINUM LAKE; FD&C YELLOW NO. 6 ALUMINUM LAKE; HYPROMELLOSE, UNSPECIFIED; MAGNESIUM STEARATE; MICROCRYSTALLINE CELLULOSE; POLYDEXTROSE; POLYETHYLENE GLYCOL, UNSPECIFIED; SILICON DIOXIDE; TITANIUM DIOXIDE; TRIACETIN

Kroger 44-112

Active ingredient (in each tablet)

Pseudoephedrine HCl 30 mg

Purpose

Nasal decongestant

Uses

- temporarily relieves nasal congestion due to the common cold, hay fever or other upper respiratory allergies
- temporarily relieves sinus congestion and pressure

Warnings

Do not use

if you are now taking a prescription monoamine oxidase inhibitor (MAOI) (certain drugs for depression, psychiatric or emotional conditions, or Parkinson's disease), or for 2 weeks after stopping the MAOI drug. If you do not know if your prescription drug contains an MAOI, ask a doctor or pharmacist before taking this product.

Ask a doctor before use if you have

- heart disease
- diabetes
- thyroid disease
- high blood pressure
- difficulty in urination due to enlargement of the prostate gland

When using this product

do not exceed recommended dosage.

Stop use and ask a doctor if

- nervousness, dizziness, or sleeplessness occur
- symptoms do not improve within 7 days or occur with fever

If pregnant or breast-feeding,

ask a health professional before use.

Keep out of reach of children.

In case of overdose, get medical help or contact a Poison Control Center right away.

Directions

adults and children 12 years and over | take 2 tablets every 4 to 6 hours; do not take more than 8 tablets in 24 hours
children ages 6 to 11 years | take 1 tablet every 4 to 6 hours; do not take more than 4 tablets in 24 hours
children under 6 years | do not use

Other information

- each tablet contains: calcium 15 mg
- TAMPER EVIDENT: DO NOT USE IF OUTER PACKAGE IS OPENED OR BLISTER IS TORN OR BROKEN
- store at 25°C (77°F); excursions permitted between 15°-30°C (59°-86°F)
- see end flap for expiration date and lot number

Inactive ingredients

croscarmellose sodium, dibasic calcium phosphate dihydrate, FD&C red #40 aluminum lake, FD&C yellow #6 aluminum lake, hypromellose, magnesium stearate, microcrystalline cellulose, polydextrose, polyethylene glycol, silicon dioxide, titanium dioxide, triacetin

Questions or comments?

Call 1-800-632-6900

Principal Display Panel

Kroger
®health

NDC 30142-641-22

COMPARE TO THE ACTIVE INGREDIENT IN
SUDAFED® SINUS CONGESTION*

MAXIMUM STRENGTH
Sinus Decongestion
Pseudoephedrine HCl 30 mg
Nasal Decongestant
SINUS PRESSURE
SINUS CONGESTION

NON-
DROWSY

ACTUAL SIZE

48 TABLETS

TAMPER EVIDENT: DO NOT USE IF PACKAGE IS OPENED OR IF BLISTER
UNIT IS TORN, BROKEN OR SHOWS ANY SIGNS OF TAMPERING

PROUDLY DISTRIBUTED BY THE KROGER CO.
CINCINNATI, OHIO 45202

‡OUR PHARMACIST RECOMMENDED

For More Product Information ,
Scan UPC Using Your Kroger App
or Call 800-632-6900

*SUDAFED® is a registered trademark of KENVUE INC.
KENVUE INC. is not affiliated with The Kroger Co. or this product.
50844 REV0619A11222

Quality Guarantee
Kroger.com/guarantee
800-632-6900

Kroger 44-112